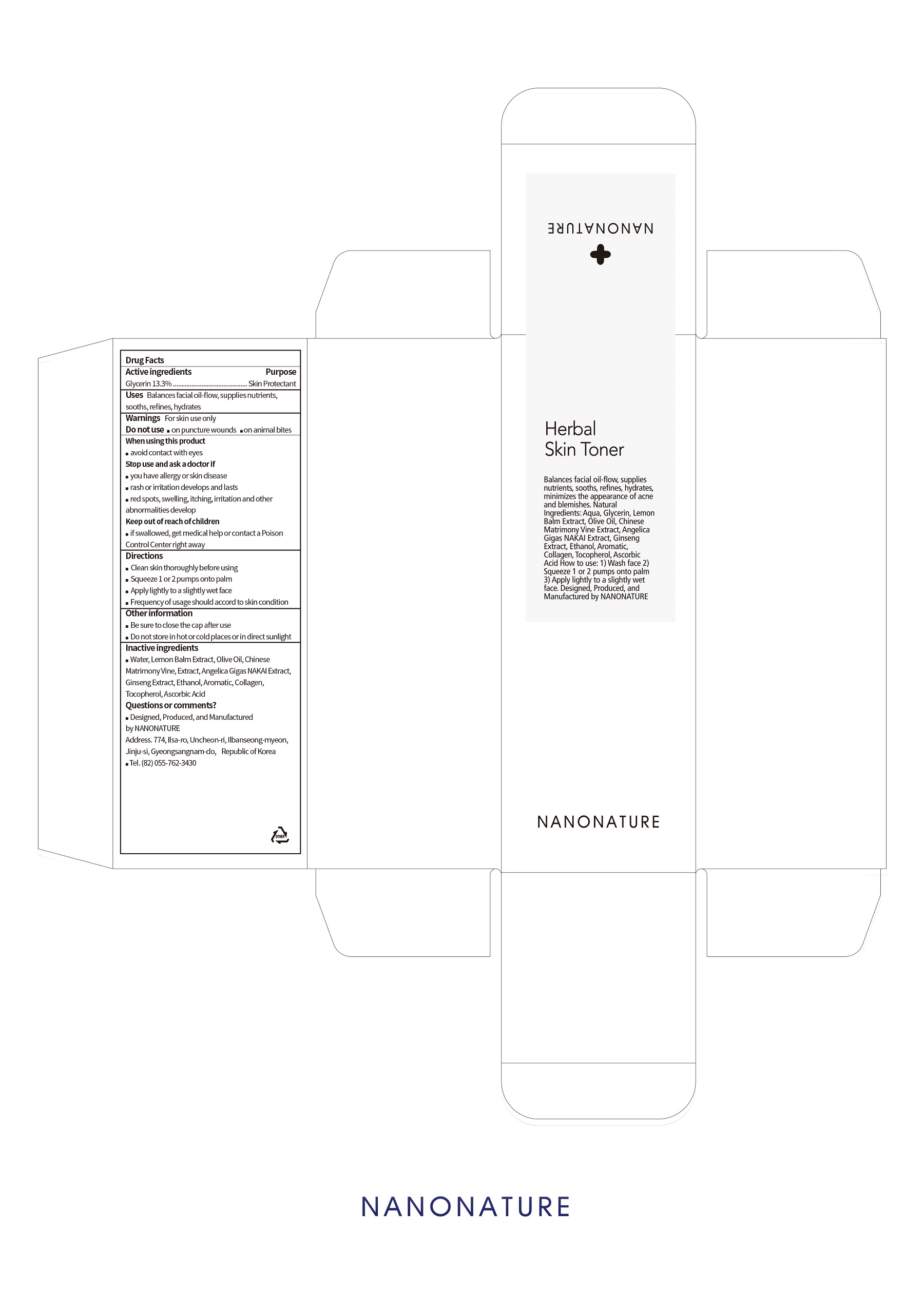 DRUG LABEL: Herbal Skin Toner
NDC: 71538-001 | Form: SOLUTION
Manufacturer: NANONATURE
Category: otc | Type: HUMAN OTC DRUG LABEL
Date: 20170717

ACTIVE INGREDIENTS: glycerin 15.96 g/120 mL
INACTIVE INGREDIENTS: Water; Olive Oil; Tocopherol

ACTIVE INGREDIENT

Glycerin (13.3%) - Skin Protectant

INACTIVE INGREDIENT

Water, Lemon Balm Extract, Olive Oil, Chinese Matrimony Vine Extract, Angelica Gigas NAKAI Extract, Ginseng Extract, Ethanol, Aromatic, Collagen, Tocopherol, Ascobic Acid

PURPOSE

Skin Protectant

WARNINGS

When using this product
 avoid contact with eyes
Stop use and ask a doctor if
 you have allergy or skin disease
 rash or irritation develops and lasts
 red spots, swelling, itching, irritation and other abnormalities develops

KEEP OUT OF REACH OF CHILDREN

 if swallowed, get medical help or contact a Poison Control Center right away

INDICATIONS & USAGE

 Clean skin thoroughly before using
 Squeeze 1 or 2 pumps onto palm
 Apply lightly to a slightly wet face
 Frequency of usage should accord to skin condition

DOSAGE & ADMINISTRATION

 Clean skin thoroughly before using
 Squeeze 1 or 2 pumps onto palm
 Apply lightly to a slightly wet face
 Frequency of usage should accord to skin condition